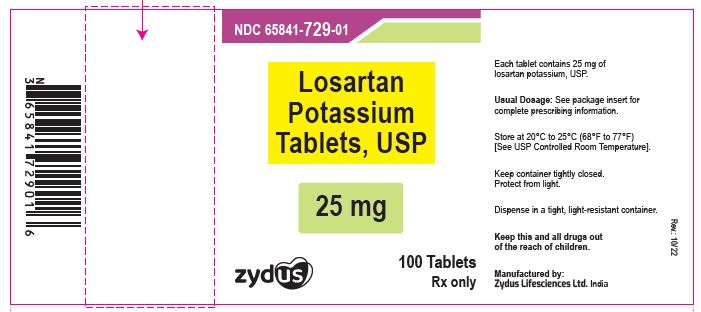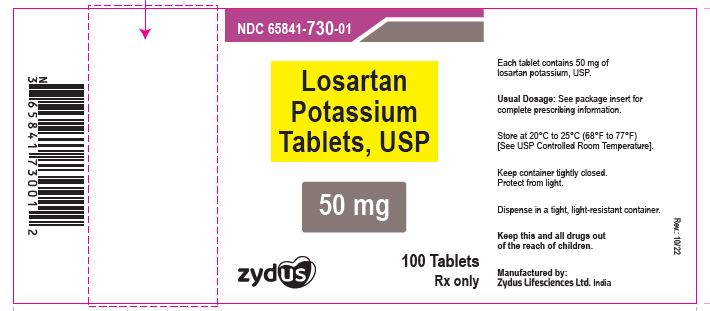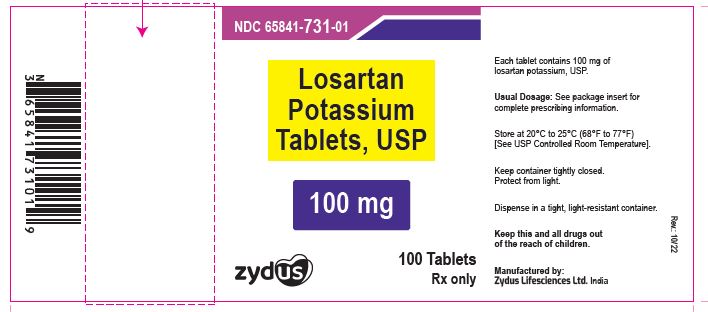 DRUG LABEL: Losartan Potassium
NDC: 65841-729 | Form: TABLET, FILM COATED
Manufacturer: Zydus Lifesciences Limited
Category: prescription | Type: HUMAN PRESCRIPTION DRUG LABEL
Date: 20260112

ACTIVE INGREDIENTS: LOSARTAN POTASSIUM 25 mg/1 1
INACTIVE INGREDIENTS: HYPROMELLOSES; LACTOSE MONOHYDRATE; MAGNESIUM STEARATE; SODIUM STARCH GLYCOLATE TYPE A POTATO; TALC; TITANIUM DIOXIDE; SILICON DIOXIDE; CELLULOSE, MICROCRYSTALLINE; HYDROXYPROPYL CELLULOSE, LOW SUBSTITUTED; STARCH, CORN; POLYETHYLENE GLYCOL, UNSPECIFIED

LOSARTAN POTASSIUM TABLETS

PACKAGE LABEL.PRINCIPAL DISPLAY PANEL

NDC 65841-729-01

Losartan Potassium Tablets USP, 25 mg

Rx Only

100 Tablets

Zydus

NDC 65841-730-01

Losartan Potassium Tablets USP, 50 mg

Rx Only

100 Tablets

Zydus

NDC 65841-731-01

Losartan Potassium Tablets USP, 100 mg

Rx Only

100 Tablets

Zydus